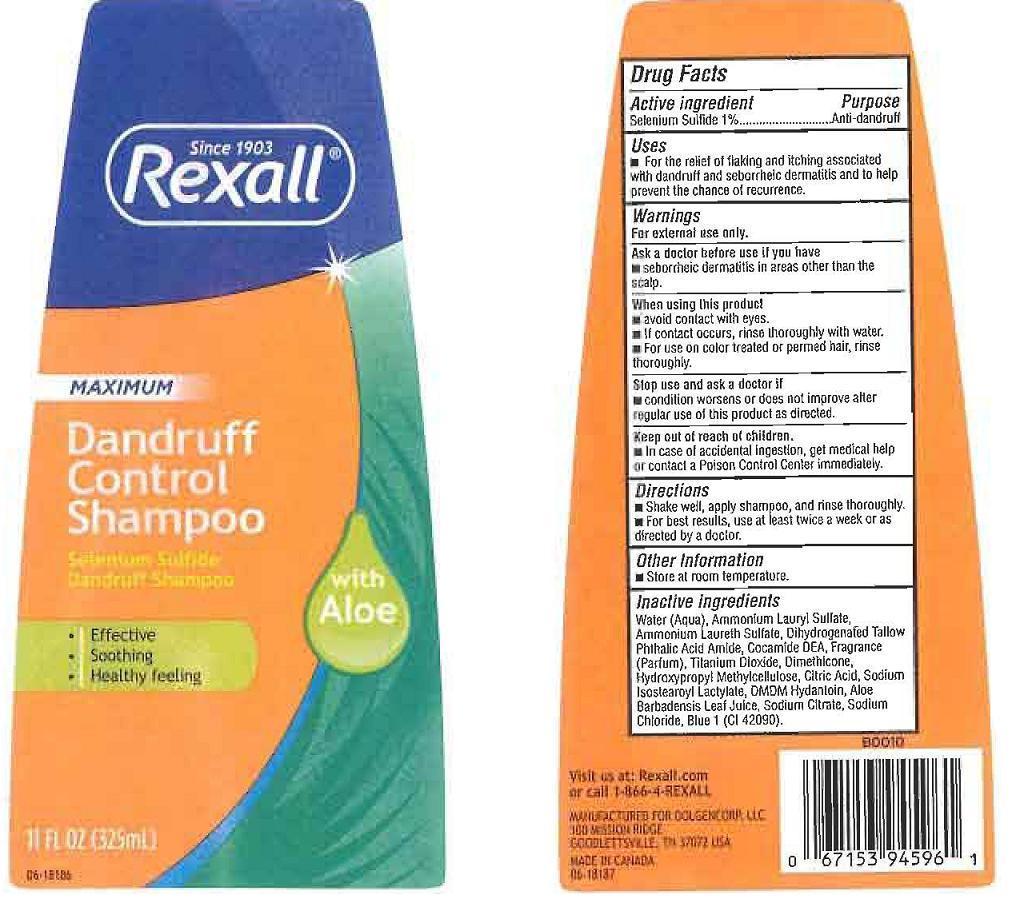 DRUG LABEL: REXALL
NDC: 55910-616 | Form: LIQUID
Manufacturer: DOLGENCORP INC.
Category: otc | Type: HUMAN OTC DRUG LABEL
Date: 20120925

ACTIVE INGREDIENTS: SELENIUM SULFIDE 1 mL/100 mL
INACTIVE INGREDIENTS: WATER; AMMONIUM LAURYL SULFATE; AMMONIUM LAURETH-3 SULFATE; DIHYDROGENATED TALLOW PHTHALIC ACID AMIDE; COCO DIETHANOLAMIDE; TITANIUM DIOXIDE; DIMETHICONE; HYPROMELLOSES; CITRIC ACID MONOHYDRATE; SODIUM ISOSTEAROYL LACTYLATE; DMDM HYDANTOIN; ALOE VERA LEAF; SODIUM CITRATE; SODIUM CHLORIDE; FD&C BLUE NO. 1

DRUG FACTS

ACTIVE INGREDIENT

SELENIUM SULFIDE 1%

PURPOSE

ANTI-DANDRUFF

USES

FOR THE RELIEF OF FLAKING AND ITCHING ASSOCIATED WITH DANDRUFF AND SEBORRHEIC DERMATITIS AND TO HELP PREVENT THE CHANCE OF RECURRENCE.

WARNINGS

FOR EXTERNAL USE ONLY.

ASK A DOCTOR BEFORE USE IF YOU HAVE

SEBORRHEIC DERMATITIS IN AREAS OTHER THAN THE SCALP.

WHEN USING THIS PRODUCT

STOP USE AND ASK A DOCTOR IF

KEEP OUT OF REACH OF CHILDREN

IN CASE OF ACCIDENTAL INGESTION, GET MEDICAL HELP OR CONTACT A POISON CONTROL CENTER IMMEDIATELY.

DIRECTIONS

SHAKE WELL, APPLY SHAMPOO, AND RINSE THOROUGHLY. FOR BEST RESULTS, USE AT LEAST TWICE A WEEK OR AS DIRECTED BY A DOCTOR.

OTHER INFORMATION

STORE AT ROOM TEMPERATURE.

INACTIVE INGREDIENTS

WATER (AQUA), AMMONIUM LAURYL SULFATE, AMMONIUM LAURETH SULFATE, DIHYDROGENATED TALLOW PHTALIC ACID AMIDE, COCAMIDE DEA, FRAGRANCE (PARFUM), TITANIUM DIOXIDE, DIMETHICONE, HYDROXYPROPYL METHYLCELLULOSE, CITRIC ACID, SODIUM ISOSTEAROYL LACTYLATE, DMDM HYDANTOIN, ALOE BARBADENSIS LEAF JUICE, SODIUM CITRATE, SODIUM CHLORIDE, BLUE 1 (CI 42090).